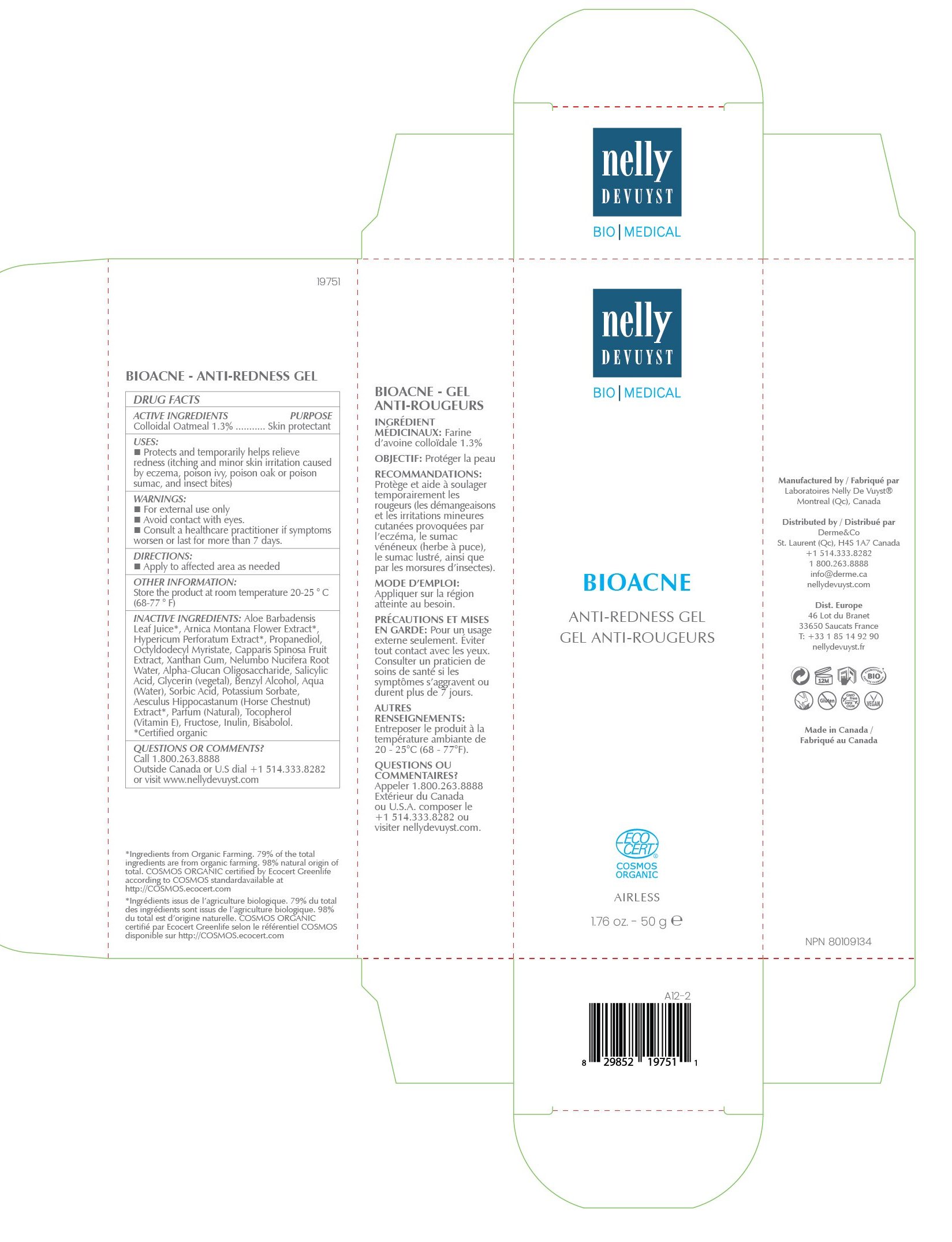 DRUG LABEL: NELLY DEVUYST BIO MEDICAL BIOACNE ANTI-REDNESS 50G
NDC: 71447-053 | Form: GEL
Manufacturer: LABORATOIRES DRUIDE INC
Category: otc | Type: HUMAN OTC DRUG LABEL
Date: 20220101

ACTIVE INGREDIENTS: OATMEAL 1.3 g/100 g
INACTIVE INGREDIENTS: LEVOMENOL; ARNICA MONTANA FLOWER; CAPER BERRY; PROPANEDIOL; NELUMBO NUCIFERA ROOT OIL; GLYCERIN; TOCOPHEROL; SALICYLIC ACID; XANTHAN GUM; BENZYL ALCOHOL; POTASSIUM SORBATE; SORBIC ACID; LAVENDER OIL; .ALPHA.-GLUCAN OLIGOSACCHARIDE; WATER; HORSE CHESTNUT; FRUCTOSE; ALOE VERA LEAF; HYPERICUM PERFORATUM; OCTYLDODECYL MYRISTATE; INULIN

NELLY DEVUYST BIO MEDICAL BIOACNE ANTI-REDNESS GEL 50 G

Active Ingredients

Colloidal Oatmeal 1.3%

Purpose

Skin Protectant

Uses

▪ Temporarily protects and helps relieve minor skin irritations and itching due to eczema rash and dermatitis.

Warnings

For external use only

Do not use

Consult a healthcare practitioner if symptoms worsen or last for more than 7 days.

When using this product

keep out of eyes. Rinse with water to remove.

Stop use and ask a doctor if

rash occurs.

Keep out of reach of children

If swallowed, get medical help or contact Poison Control Center right away.

Directions

▪ Apply to affected area as needed.

Other Information

Protect the product in this container from excessive heat and direct sun. Store the product at room temperature 20 to 25°C (68 to 77°F).

Inactive Ingredients

Aloe Barbadensis Leaf Juice*, Arnica Montana Flower Extract*, Hypericum Perforatum Extract*, Propanediol, Octyldodecyl Myristate, Capparis Spinosa Fruit Extract, Xanthan Gum, Nelumbo Nucifera Root Water, Alpha-Glucan Oligosaccharide, Salicylic Acid, Glycerin (vegetal), Benzyl Alcohol, Aqua (Water), Sorbic Acid, Potassium Sorbate, Aesculus Hippocastanum (Horse Chestnut) Extract*, Parfum (Natural), Tocopherol (Vitamin E), Fructose, Inulin, Bisabolol.

*Certified organic.

Questions or Comments?

1-800-263-8888

Outside Canada or the United States dial 514-333-8282 or visit www.nellydevuyst.com